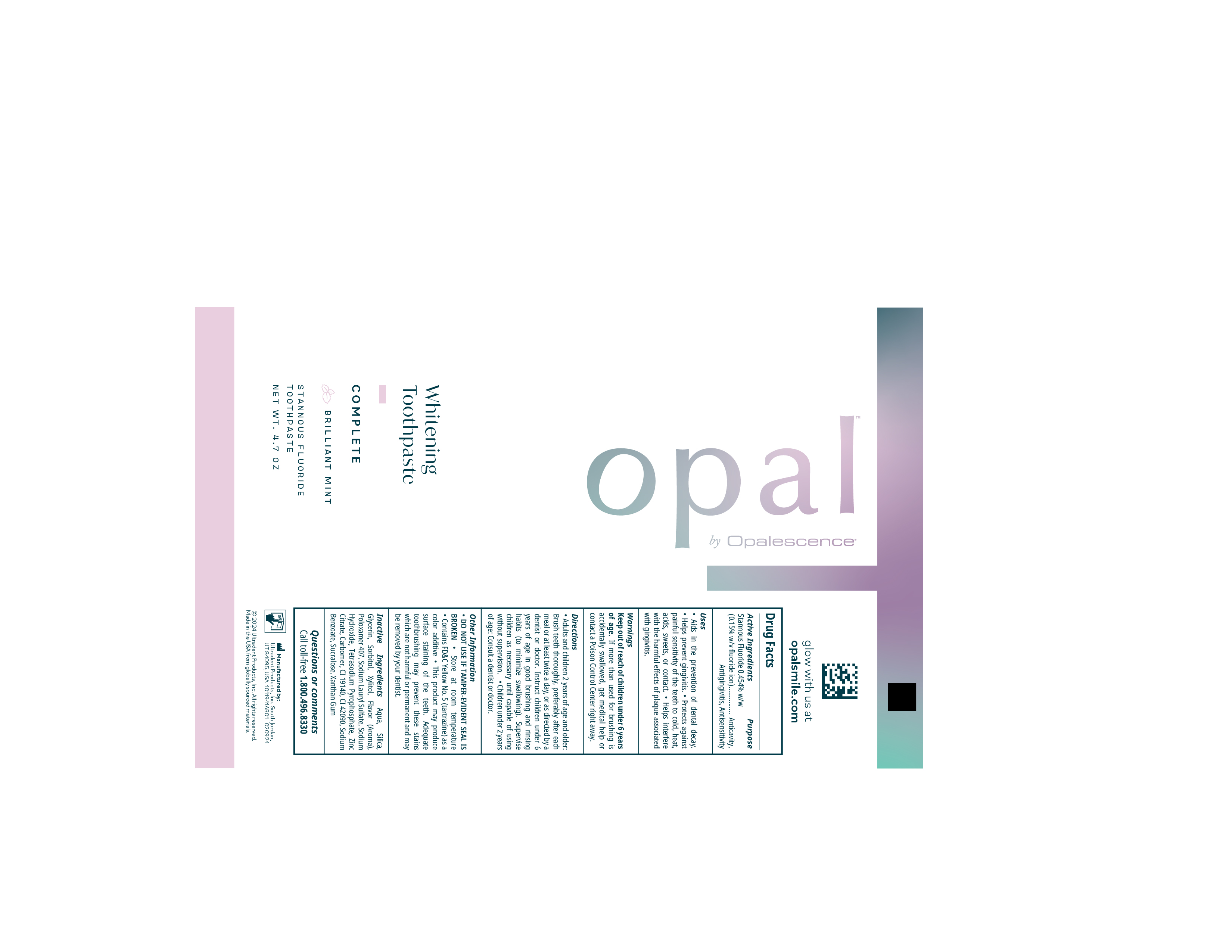 DRUG LABEL: Opal by Opalescence Complete
NDC: 51206-313 | Form: GEL, DENTIFRICE
Manufacturer: Ultradent Products, Inc.
Category: otc | Type: HUMAN OTC DRUG LABEL
Date: 20250617

ACTIVE INGREDIENTS: STANNOUS FLUORIDE 1.1 mg/1 g
INACTIVE INGREDIENTS: FLAVOR SPICE MINT N&A110589; ZINC CITRATE; FD&C BLUE NO. 1; SODIUM HYDROXIDE; SODIUM LAURYL SULFATE; WATER; XYLITOL; POLOXAMER 407; SODIUM PYROPHOSPHATE; SODIUM BENZOATE; XANTHAN GUM; CARBOMER HOMOPOLYMER TYPE B (ALLYL PENTAERYTHRITOL CROSSLINKED); GLYCERIN; SUCRALOSE; SILICON DIOXIDE; FD&C YELLOW NO. 5; SORBITOL

Keep out of reach of children under 6 years of age. If more than used for burshing is accidentally swallowed, get medical help or contact a Poison Control Center right away.